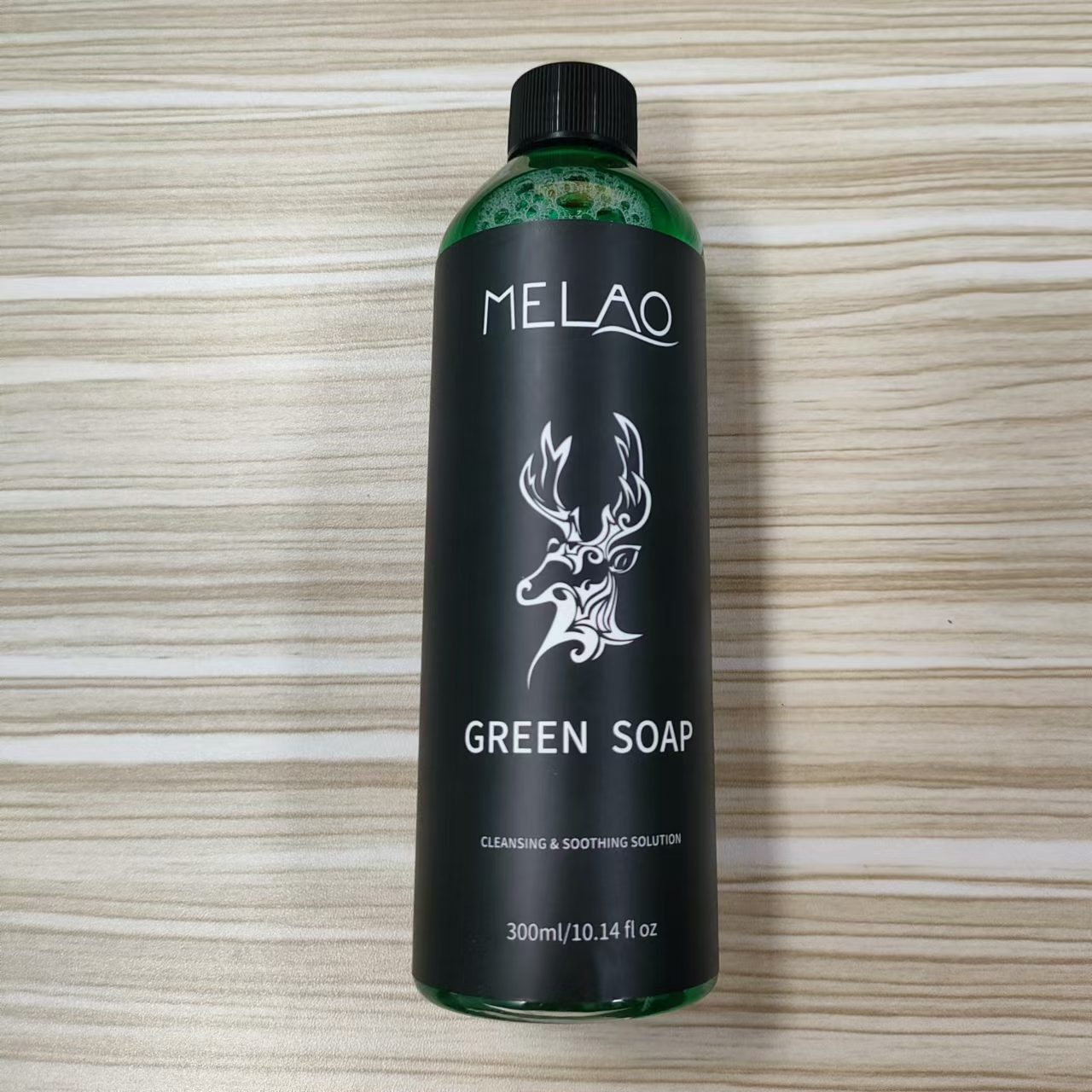 DRUG LABEL: MELAO GreenSoap
NDC: 74458-510 | Form: LIQUID
Manufacturer: Guangzhou Yilong Cosmetics Co., Ltd
Category: otc | Type: HUMAN OTC DRUG LABEL
Date: 20241126

ACTIVE INGREDIENTS: CHRYSANTHELLUM INDICUM FLOWER 1 g/100 mL; SOPHORA FLAVESCENS ROOT 1 g/100 mL; ALOE BARBADENSIS LEAF EXTRACT 1 g/100 mL; PORTULACA OLERACEA LEAF 1 g/100 mL
INACTIVE INGREDIENTS: PROPYLENE GLYCOL; COCAMIDOPROPYL BETAINE; CITRIC ACID MONOHYDRATE; PHENOXYETHANOL; WATER; MENTHA ARVENSIS LEAF; CI 19140; GLYCERIN; SODIUM LAUROYL SARCOSINATE; CHLORPHENESIN; CI 42090; SODIUM LAUROYL GLUTAMATE

MELAO GREEN SOAP

ACTIVE INGREDIENT

Aloe Barbadensis Leaf Extract

1%

Portulaca Oleracea Extract

1%

Chrysanthellum Indicum Extract

1%

Sophora Angustifolia Root Extract

1%

INACTIVE INGREDIENT

Water

C12-18 Alkyl Glucoside

Sodium Lauroyl Sarcosinate

Sodium Lauroyl Glutamate

Propylene Glycol

Glycerin

Cocamidopropyl Betaine

Mentha Arvensis Leaf Extract

Hydrangea Macrophyla Leaf Extract

Citric Acid

Chlorphenesin

Phenoxyethanol

CI 42090

CI 19140

PURPOSE

Cleanses and smoothes the skin

INDICATIONS AND USAGE

Scrubbing the tattoo
with a tattoo cleaning solution after the tattoo

WARNINGS

For external use only.

Stop use and ask a doctor if rash occurs.

Do not use on damaged or broken skin.

When using this product keep out of eyes. Rinse with water to remove.

Keep out of reach of children. If swallowed, get medical help or contact a Poison Control Center right away.

DOSAGE AND ADMINISTRATION

Scrubbing the tattoo
with a tattoo cleaning solution after the tattoo